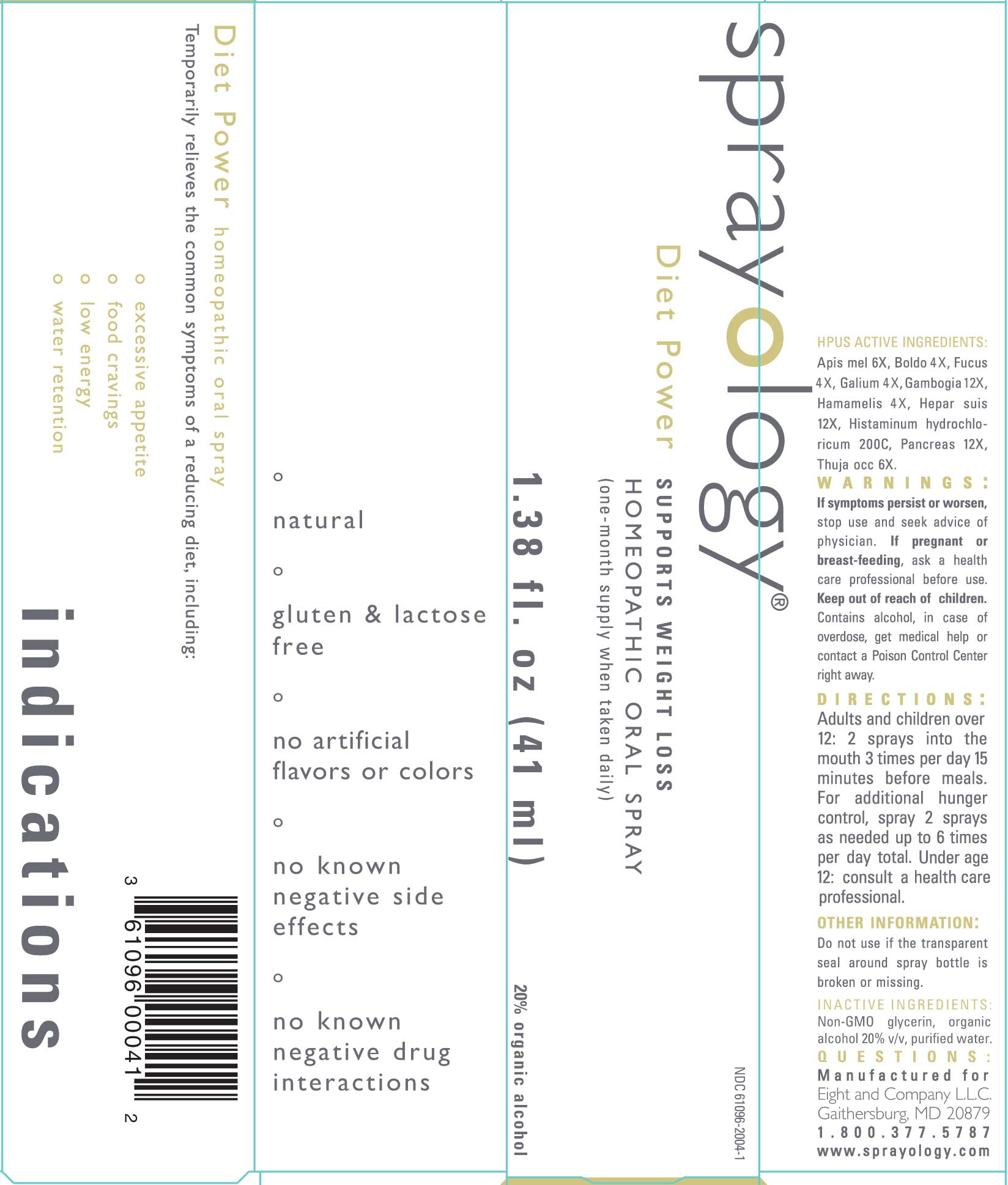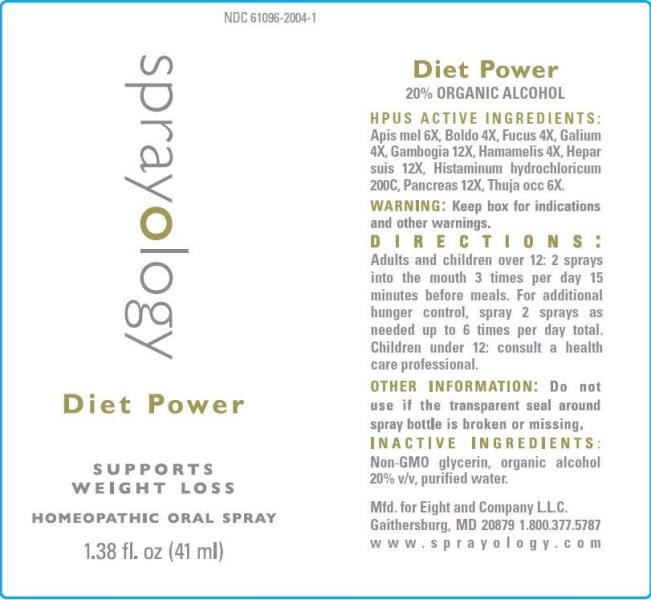 DRUG LABEL: Diet Power
NDC: 61096-2004 | Form: LIQUID
Manufacturer: Eight and Company L.L.C
Category: homeopathic | Type: HUMAN OTC DRUG LABEL
Date: 20251218

ACTIVE INGREDIENTS: APIS MELLIFERA 6 [hp_X]/1 mL; PEUMUS BOLDUS LEAF 4 [hp_X]/1 mL; FUCUS VESICULOSUS 4 [hp_X]/1 mL; GALIUM APARINE WHOLE 4 [hp_X]/1 mL; GAMBOGE 12 [hp_X]/1 mL; HAMAMELIS VIRGINIANA ROOT BARK/STEM BARK 4 [hp_X]/1 mL; PORK LIVER 12 [hp_X]/1 mL; HISTAMINE DIHYDROCHLORIDE 200 [hp_C]/1 mL; SUS SCROFA PANCREAS 12 [hp_X]/1 mL; THUJA OCCIDENTALIS LEAFY TWIG 6 [hp_X]/1 mL
INACTIVE INGREDIENTS: GLYCERIN; ALCOHOL; Water

Diet Power

ACTIVE INGREDIENTS:

Apis Mellifica 6X, Boldo 4X, Fucus Vesiculosus 4X, Galium Aparine 4X, Gambogia 12X, Hamamelis Virginiana 4X, Hepar Suis 12X, Histaminum hydrochloricum 200C, Pancreas Suis 12X, Thuja Occidentalis 6X.

PURPOSE:

Temporarily relieves the common symptoms of a reducing diet, including:

° excessive appetite
° food cravings
° low energy
° water retention

WARNINGS:

If symptoms persist or worsen, seek advice of physician. If pregnant or breast-feeding, ask a health care professional before use. Keep out of reach of children. Contains alcohol, in case of overdose, get medical help or contact a Poison Control Center right away.

Keep out of reach of children. Contains alcohol, in case of overdose, get medical help or contact a Poison Control Center right away.

DIRECTIONS:

Adults and children over 12: 2 sprays into the mouth 3 times per day 15 minutes before meals. For additional hunger control, spray 2 sprays as needed up to 6 times per day total.

Under age 12: consult a health care professional.

OTHER INFORMATION:

Do not use if the transparent seal around spray bottle is broken or missing.

INDICATIONS:

Temporarily relieves the common symptoms of a reducing diet, including:

° excessive appetite

° food cravings

° low energy

° water retention

° natural

° gluten & lactose free

° no artificial flavors or colors

° no known negative side effects

° no known negative drug interactions

INACTIVE INGREDIENTS:

Non-GMO Glycerin, organic alcohol 20% v/v, purified water.

QUESTIONS:

Mfd. for Eight and Company L.L.C.

Gaithersburg, MD 20879 1.800.377.5787

www.sprayology.com

PACKAGE LABEL DISPLAY:

NDC 61096-2004-1

sprayology

Diet Power

SUPPORTS WEIGHT LOSS

HOMEOPATHIC ORAL SPRAY

1.38 fl.oz (41 ml)